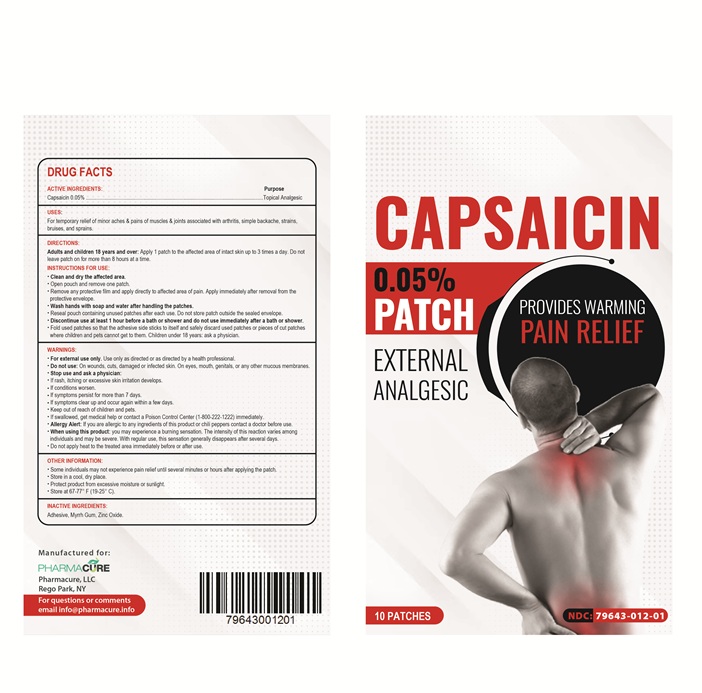 DRUG LABEL: Capsaicin
NDC: 79643-012 | Form: PATCH
Manufacturer: PHARMACURE LLC
Category: otc | Type: HUMAN OTC DRUG LABEL
Date: 20250828

ACTIVE INGREDIENTS: CAPSAICIN 0.05 g/100 g
INACTIVE INGREDIENTS: MYRRH; ZINC OXIDE

Active Ingredient Purpose

Capsaicin 0.05% Topical Analgesic

Uses

Temporarily relieves minor aches and pains of muscles and joints associated with arthritis, simple backache, bruises, sprains, and strains

Warnings

For external use only. Use only as directed or as directed by a health care professional.

Do not use

• On wounds, cuts, damaged, or infected skin

• On eyes, mouth, genitals, or any other mucous membranes

Stop use and ask a physician:

- If rash, itching, or excessive skin irritation develops.
- If conditions worsen.
- If symptoms persist for more than 7 days.
- If symptoms clear up and occur again within a few days.
- Keep out of reach of children and pets.
- If swallowed, get medical help or contact a Poison Control Center (1-800-222-1222) immediately.
- Allergy Alert: If you are allergic to capsicum or chili peppers or any inactive ingredient of this product, contact a doctor before use.

When using this product

You may experience a burning sensation. The intensity of this reaction varies among individuals and may be severe. With regular use, this sensation generally disappears after several days.

• Do not apply heat to the treated area immediately before or after use

Directions

Adults and children 18 years of age and older: Apply 1 patch to the affected area of intact skin up to 3 times a day. Do not leave the patch on for more than 8 hours at a time.

Instructions for use:

- Clean and dry the affected area.
- Open the pouch and remove one patch.
- Remove any protective film and apply directly to the affected area of pain. Apply immediately after removal from the protective envelope.

- Wash your hands with soap and water after handling the patches.

- Reseal pouch containing unused patches after each use. Do not store the patch outside the sealed envelope.
- Fold used patches so that the adhesive side sticks to itself and safely discard used patches or pieces of cut patches where children and pets cannot get to them.

Children under 18 years: Ask a physician

Other Information

- Some individuals may not experience pain relief until several minutes or hours after applying the patch.
- Store in a cool and dry place.
- Store at 67°-77°F (19°-25° C)
- Protect the product from excessive moisture or sunlight.

Inactive ingredients

Adhesive, myrrh gum, zinc oxide